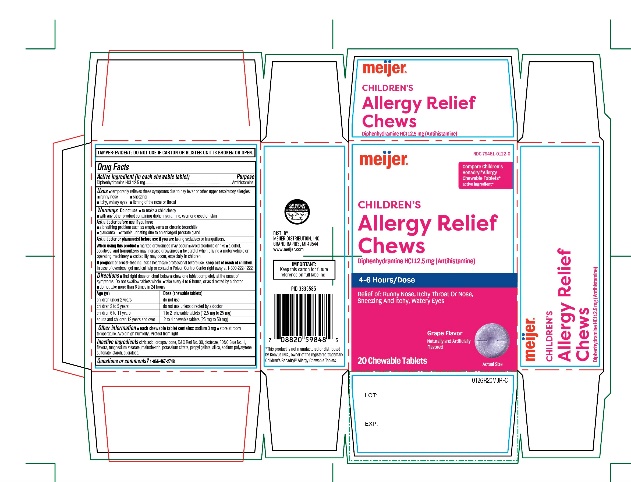 DRUG LABEL: MEIJER
NDC: 79481-0122 | Form: TABLET, CHEWABLE
Manufacturer: MEIJER DISTRIBUTION INC
Category: otc | Type: HUMAN OTC DRUG LABEL
Date: 20260227

ACTIVE INGREDIENTS: DIPHENHYDRAMINE HYDROCHLORIDE 12.5 mg/1 1
INACTIVE INGREDIENTS: CITRIC ACID MONOHYDRATE; CROSPOVIDONE (120 .MU.M); D&C RED NO. 30; DEXTROSE, UNSPECIFIED FORM; FD&C BLUE NO. 1; MAGNESIUM STEARATE; MALTODEXTRIN; POTASSIUM CITRATE; SILICON DIOXIDE; SODIUM POLYSTYRENE SULFONATE; STARCH, CORN; SUCRALOSE

MEIJER Children’s Allergy Relief Chews

Active ingredient (in each chewable tablet)

Diphenhydramine HCl 12.5 mg

Purpose

Antihistamine

Uses

- temporarily relieves these symptoms due to hay fever or other upper respiratory allergies.
  - runny nose
  - itchy, watery eyes
  - sneezing
  - itching of the nose or throat

Warnings

Do not use

- to make a child sleepy
- with any other product containing diphenhydramine, even one used on skin

Ask a doctor before use if you have

- a breathing problem such as emphysema or chronic bronchitis
- glaucoma
- trouble urinating due to an enlarged prostate gland

Ask a doctor or pharmacist before use if you are

taking sedatives or tranquilizers.

When using this product

- marked drowsiness may occur
- avoid alcoholic drinks
- alcohol, sedatives, and tranquilizers may increase drowsiness
- be careful when driving a motor vehicle or operating machinery
- excitability may occur, especially in children

If pregnant or breast-feeding,

ask a health professional before use.

Keep out of reach of children.

In case of overdose, get medical help or contact a Poison Control Center right away at 1-800-222-1222

Directions

- find right dose on chart below
- Chew one tablet completely at the onset of symptoms. Do not swallow tablets whole.
- take every 4 to 6 hours or as directed by a doctor
- do not take more than 6 times in 24 hours

Age (Yr) | Dose (Chewable tablets)
children under 2 years | do not use
children 2 to 5 years | do not use unless directed by a doctor
children 6 to 11 years of age | 1 to 2 chewable tablets (12.5 mg to 25 mg)
adults and children 12 years of age and over | 2 to 4 tablets (25 mg to 50 mg)

Other information

- each chewable tablet contains : sodium 3 mg
- store at room temperature. Avoid high humidity. Protect from light

Inactive ingredients

citric acid, crospovidone, D&C Red No. 30, dextrose, FD&C Blue No. 1, flavors, magnesium stearate, maltodextrin, potassium citrate, silica, sodium polystyrene sulfonate, starch, sucralose.

Questions or comments?

1-866-467-2748

Principal Display Panel

Compare Children's Benadryl® Allergy Chewable Tablets*active ingredient*

NDC 79481-0122-0

CHILDREN’S

Allergy Relief Chews
Diphenhydramine HCl (Antihistamine)

4-6 Hours/Dose

Relief of : Runny nose, itchy throat or nose, sneezing and itchy, watery eyes

Grape Flavor

Naturally and Artificially Flavored

20 Chewable Tablets

TAMPER EVIDENT: DO NOT USE IF CARTON OR IF BLISTER UNIT IS BROKEN OR OPEN.

IMPORTANT: Keep this carton for future reference on full labeling.

*This product is not manufactured or distributed by Kenvue INC., owner of the registered trademark Children's Benadryl® Allergy Chewable Tablets.

DIST. BY: MEIJER DISTRIBUTION, INC.

GRAND RAPIDS, MI 49544

www.meijer.com